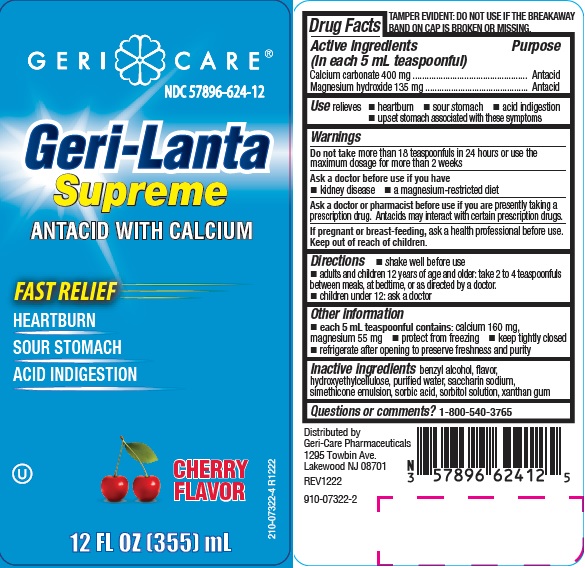 DRUG LABEL: GERI-LANTA SUPREME CHERRY
NDC: 57896-624 | Form: SUSPENSION
Manufacturer: Geri-Care Pharmaceuticals, Corp
Category: otc | Type: HUMAN OTC DRUG LABEL
Date: 20231108

ACTIVE INGREDIENTS: MAGNESIUM HYDROXIDE 135 mg/5 mL; CALCIUM CARBONATE 400 mg/5 mL
INACTIVE INGREDIENTS: BENZYL ALCOHOL; HYDROXYETHYL CELLULOSE, UNSPECIFIED; WATER; SACCHARIN SODIUM; DIMETHICONE; SORBIC ACID; SORBITOL SOLUTION; XANTHAN GUM

624 gc supreme cherry

Active ingredients (in each 5 mL teaspoonful)

Calcium carbonate 400 mg
Magnesium hydroxide 135 mg

Purpose

Antacid

Uses

relieves

- heartburn
- sour stomach
- acid indigestion
- upset stomach associated with these symptoms

Warnings

Do not take more than 18 teaspoonfuls in 24 hours or use the
maximum dosage for more than 2 weeks

Ask a doctor before use if you have

- kidney disease
- a magnesium-restricted diet

Ask a doctor or pharmacist before use if you are taking a prescription drug.
Antacids may interact with certain prescription drugs.
If pregnant or breast-feeding, ask a health professional before use.

Keep out of reach of children.

Directions

- shake well before use
- adults and children 12 years and older: take 2 to 4 teaspoonfuls between meals, at bedtime, or as directed by a doctor
- children under 12 years: ask a doctor

Other information

- each 5 mL teaspoonful contains: calcium 160mg, magnesium 55 mg
- refrigerate after opening to preserve freshness and purity
- protect from freezing
- keep tightly closed

Inactive ingredients

benzyl alcohol, flavor, hydroxyethylcellulose, purified water, saccharin sodium, simethicone emulsion, sorbic acid, sorbitol solution, xanthan gum

Questions or comments?

1-800-540-3765